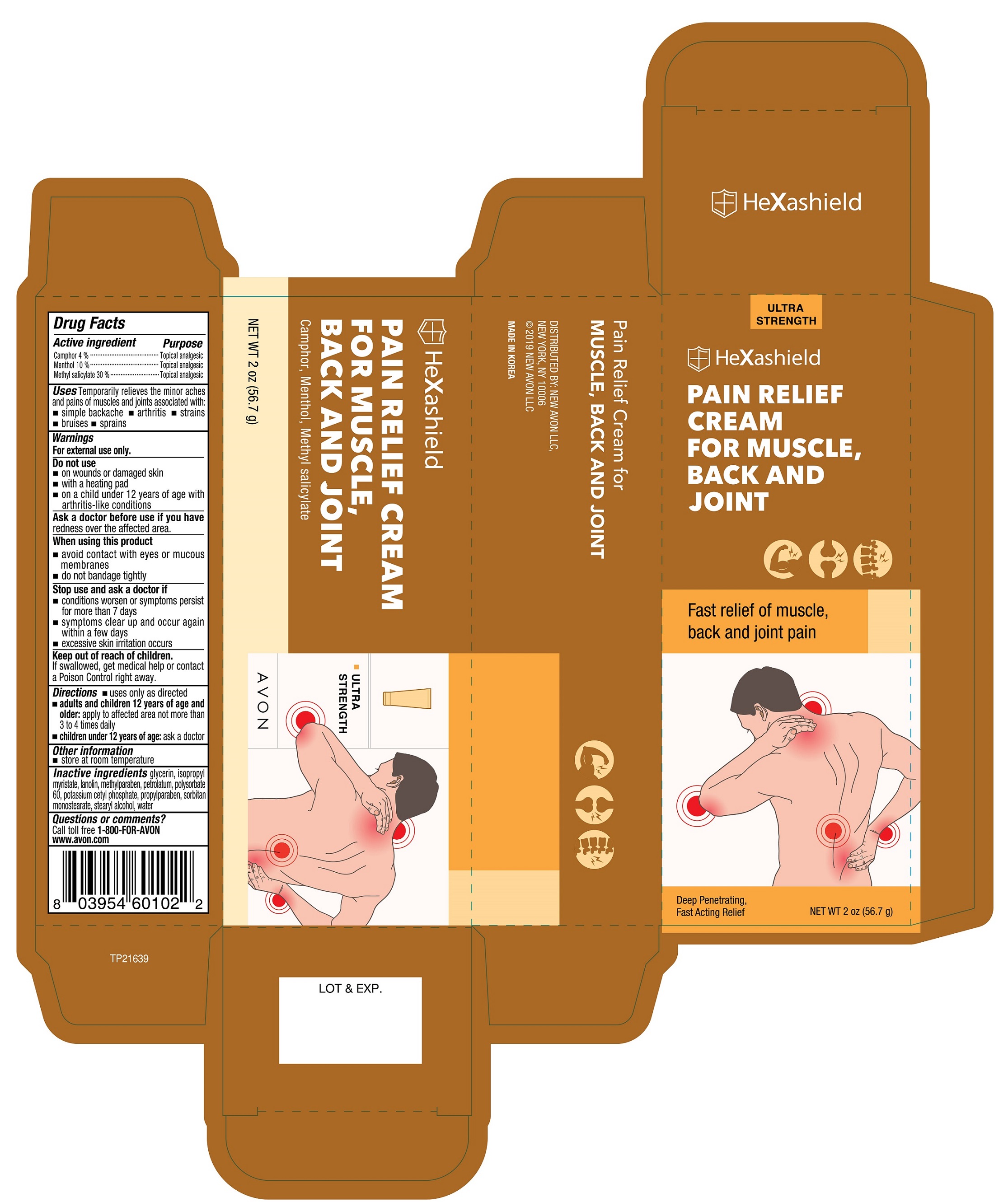 DRUG LABEL: AVON HeXashield Pain Relief for Muscle, Back and Joint
NDC: 43136-102 | Form: CREAM
Manufacturer: Tai Guk Pharm. Co., Ltd.
Category: otc | Type: HUMAN OTC DRUG LABEL
Date: 20250101

ACTIVE INGREDIENTS: LEVOMENTHOL 100 mg/1 g; METHYL SALICYLATE 300 mg/1 g; CAMPHOR (SYNTHETIC) 40 mg/1 g
INACTIVE INGREDIENTS: STEARYL ALCOHOL; WATER; PETROLATUM; ALCOHOL; POLYSORBATE 60; SORBITAN MONOSTEARATE; ISOPROPYL MYRISTATE; POTASSIUM CETYL PHOSPHATE; GLYCERIN; LANOLIN; METHYLPARABEN; PROPYLPARABEN

AVON HeXashield Pain Relief Cream for Muscle, Back And Joint

Active Ingredient

Camphor 4 %

Menthol 10 %

Methyl salicylate 30 %

Purpose

Topical analgesic

Uses

Temporary relieves the minor aches and pains of muscles and joints associated with:

- simple backache
- arthritis
- strains
- bruises
- sprains

Warnings

For external use only.

Do not use

- on wounds or damaged skin
- with a heating pad
- on a child under 12 years of age with arthritis-like conditions

Ask a doctor before use if you have

redness over the affected area.

When using this product

- avoid contact with eyes or mucous membranes
- do not banage tightly

Stop use and ask a doctor if :

- condition worsens or symptoms persist for more than 7 days
- symptoms clear up and occur again within a few days
- excessive skin irritation occurs

Keep out of reach of children.

If swallowed, get medical help or contact a Poison Control Center right away.

Directions

- use only as directed
- adults and children 12 years of age and older: apply to affected area not more than 3 to 4 times daily
- children under 12 years of age :ask a doctor

Other information

- store at room temperature

Inactive Ingredients

glycerin, isopropyl myristate, lanolin, methylparaben, petrolatum, polysorbate 60, potassium cetyl phosphate, propylparaben, sorbitan monostearate, stearyl alcohol water

Questions or comments?

Call toll free 1-800-FOR-AVON

www.avon.com

Principal Display Panel

HeXasheild

PAIN RELIEF CREAM

FOR MUSCLE,

BACK AND JOINT

Camphor, Menthol, Methyl salicylate

Fast relief of muscle, back and joint pain

Deep Penetrating, Fast Acting Relief

ULTRA STRENGTH

AVON

NET WT 2 oz (56.7 g)